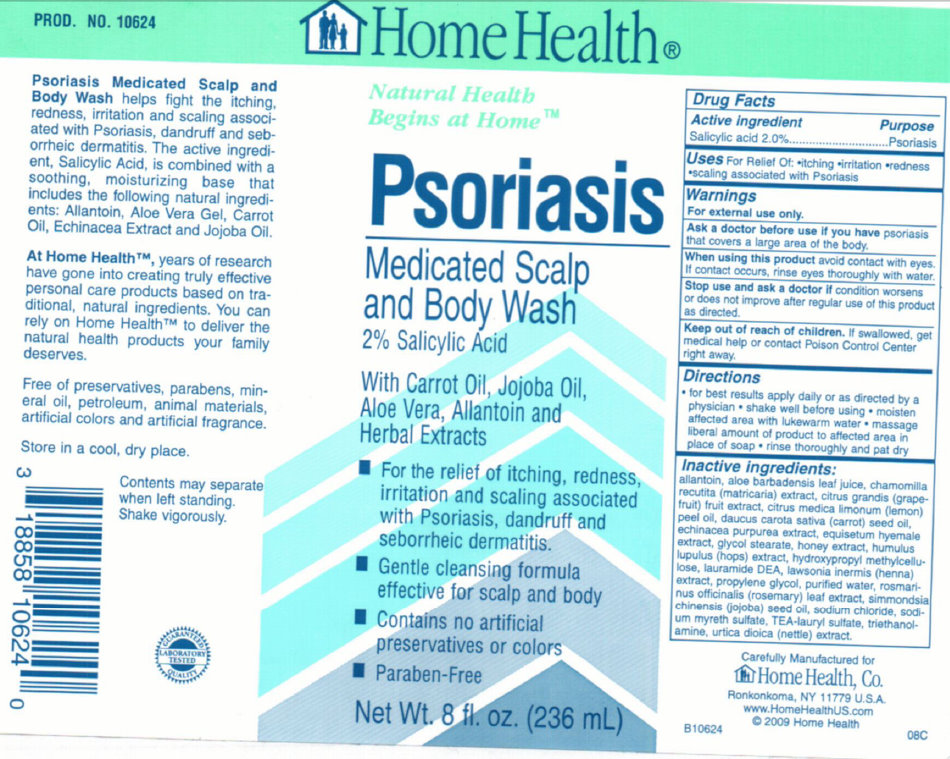 DRUG LABEL: Home Health Psoriasis Medicated Scalp and Body Wash
NDC: 76020-300 | Form: LIQUID
Manufacturer: Home Health
Category: otc | Type: HUMAN OTC DRUG LABEL
Date: 20231106

ACTIVE INGREDIENTS: SALICYLIC ACID 2 g/100 mL
INACTIVE INGREDIENTS: ALLANTOIN; ALOE VERA LEAF; CHAMOMILE; CARROT SEED OIL; ECHINACEA PURPUREA; EQUISETUM HYEMALE; GLYCOL STEARATE; HONEY; LAURIC DIETHANOLAMIDE; PROPYLENE GLYCOL; WATER; JOJOBA OIL; SODIUM CHLORIDE; TRIETHANOLAMINE LAURYL SULFATE; TROLAMINE; URTICA DIOICA LEAF

Home Health Psoriasis Medicated Scalp and Body Wash

Active Ingredient Purpose Salicylic acid 2.0% ....................Psoriasis

PURPOSE

Uses For Relief Oil -itching -irritation -redness -scaling associated with Psoriasis

Warnings For external use only.

Ask a doctor before use if you have psoriasis that covers a large area of the body.

When using this product avoid contact with eyes. If contact occurs, rinse eyes thoroughly with water.

Stop use and ask a doctor if condition worsens or does not improve after regular use of this product as directed.

Keep out of reach of children. If swallowed, get medical help or contact a Poison Control Center right away.

DOSAGE AND ADMINISTRATION

Directions -for best results apply daily or as directed by a physician - shake well before using - moisten affected area with lukewarm water - massage liberal amount of product to affected area in place of soap - rinse thoroughly and pat dry

INACTIVE INGREDIENT

Inactive ingredients: allantoin, aloe barbadensis leaf juice, chamomilla recutita (matricaria) extract, citrus grandis (grapefruit) fruit extract, citrus medica limonum (lemon) peel oil, daucus carota sativa (carrot) seed oil, echinacea purpurea extract, equisetum hyemale extract, glycol stearate, honey extract, humulus lupulus (hops) extract, hydroxypropyl methylcellulose, lauramide DEA, lawsonia inermis (henna) extract, propylene glycol, purified water, rosmarinus officinalis (rosemary) leaf extract, simmondsia chinensis (jojoba) seed oil, sodium chloride, sodium myreth sulfate, TEA-lauryl sulfate, triethanolamine, urtica dioica (nettle) extract.

DESCRIPTION

PROD. NO. 10624 Psoriasis Medicated Scalp and Body Wash helps fight the itching, redness, irritation and scaling associated with Psoriasis, dandruff and seborrheic dermatitis. The active ingredient, Salicylic Acid, is combined with a soothing, moisturizing base that includes the following natural ingredients: Allantoin, Aloe Vera Gel, Carrot Oil, Echinacea Extract and Jojoba Oil. At Home Health, years of research have gone into creating truly effective personal care products based on traditional, natural ingredients. You can rely on Home Health to deliver the natural health products your family deserves. Free of preservatives, parabens, mineral oil, petroleum, animal materials, artificial colors and artificial fragrance. Store in a cool, dry place. Contents may separate when left standing. Shake vigorously. GUARANTEED LABORATORY TESTED QUALITY 3 18858 10624 0 Carefully Manufactured for Home Health, Co. Ronkonkoma, NY 11779 U.S.A www.HomeHealthUS.com C2009 Home Health B10624 08C

PACKAGE LABEL

Home Health Natural Health Begins at Home Psoriasis Medicated Scalp and Body Wash 2% Salicylic Acid With Carrot Oil, Jojoba Oil, Aloe Vera, Allantoin and Herbal Extracts - For the relief of itching, redness, irritation and scaling associated with Psoriasis, dandruff and seborrheic dermatitis. - Gentle cleansing formula effective for scalp and body - Contains no artificial preservatives or colors - Paraben-Free Net WT. 8 fl. oz. (236 mL)